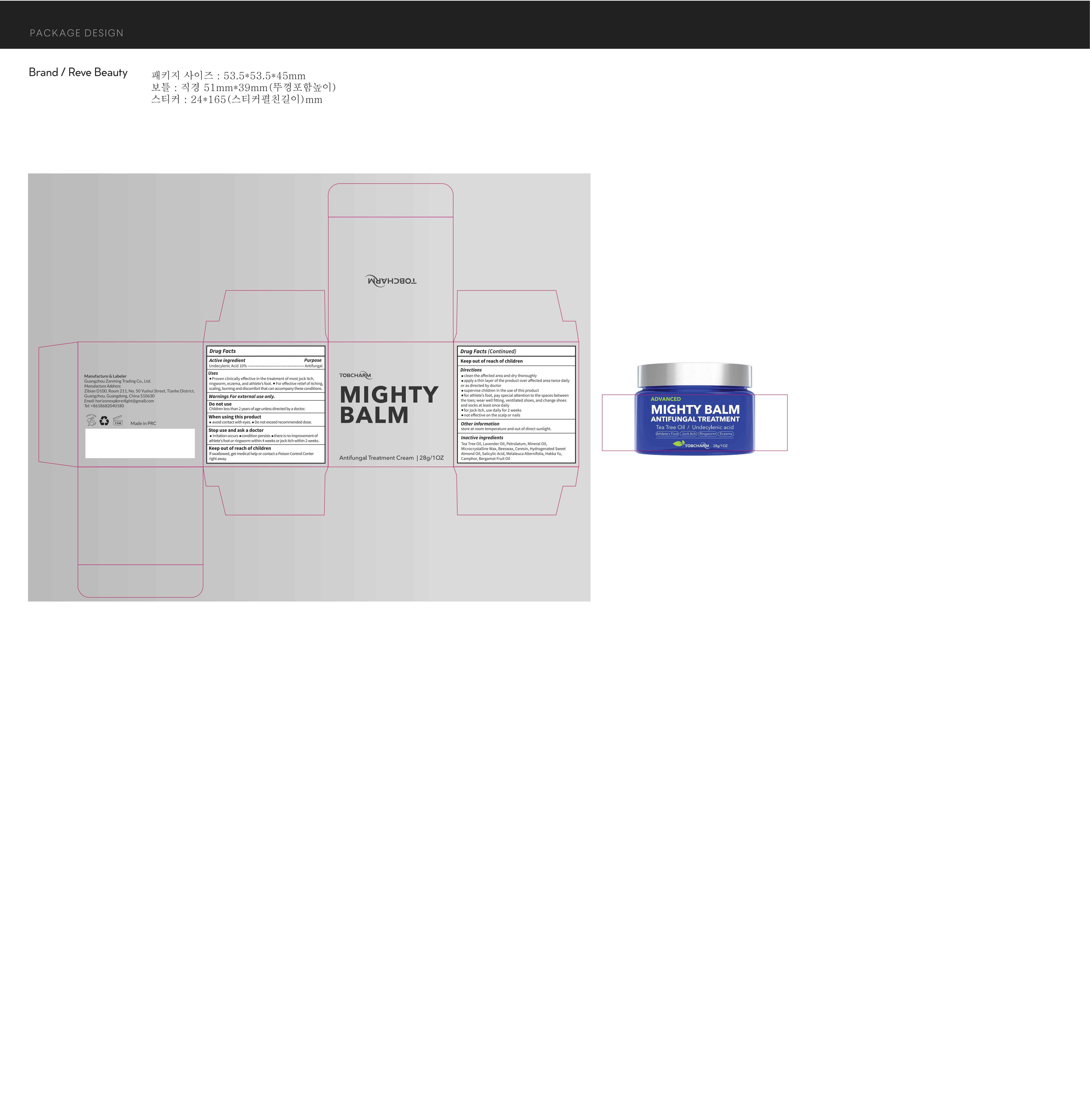 DRUG LABEL: Tobcharm Antifungal Treatment Cream
NDC: 85150-002 | Form: CREAM
Manufacturer: Guangzhou Zanming Trading Co., Ltd.
Category: otc | Type: HUMAN OTC DRUG LABEL
Date: 20250113

ACTIVE INGREDIENTS: UNDECYLENIC ACID 10 g/100 g
INACTIVE INGREDIENTS: MICROCRYSTALLINE WAX; ALMOND OIL; BERGAMOT OIL; MENTHA ARVENSIS LEAF; SIMMONDSIA CHINENSIS (JOJOBA) SEED OIL; PETROLATUM; BEESWAX; CAMPHOR (SYNTHETIC); CERESIN; SALICYLIC ACID; TEA TREE OIL; LAVENDER OIL

85150-002

Active Ingredient

Undecylenic Acid 10%

Purpose

Anti fungal

Use

1 Proven clinically effective in the treatment of most jock itch, ringworm, eczema, and athlete's foot.

2 For effective relief of itching, scaling, burning and discomfort that can accompany these conditions.

Warnings

For external use only.

Do not use

Children less than 2 years of age unless directed by a doctor.

When Using

• Avoid contact with eyes.

• Do not exceed recommended dose.

Stop Use

irritation occurs or a condition persists

Ask Doctor

there is no improvement of athlete's foot or ringworm within 4 weeks or jock itch within 2 weeks.

Keep Oot Of Reach Of Children

If swallowed, get medical help or contact a Poison Control Center right away.

Directions

• clean the affected area and dry thoroughly
• apply a thin layer of the product over affected area twice daily or as directed by doctor
• supervise children in the use of this product
• for athlete's foot, pay special attention to the spaces between the toes; wear well fitting, ventilated shoes, and change shoes and socks at least once daily
• for jock itch, use daily for 2 weeks
• not effective on the scalp or nails

Other information

store at room temperature and out of direct sunlight.

Inactive ingredients

Tea Tree Oil, Lavender Oil, Petrolatum, Mineral Oil.Microcrystalline Wax, Beeswax, Ceresin, Hydrogenated Sweet Almond Oil, Salicylic Acid, Melaleuca Alternifolia, Hakka Yu.Camphor, Bergamot Fruit Oil